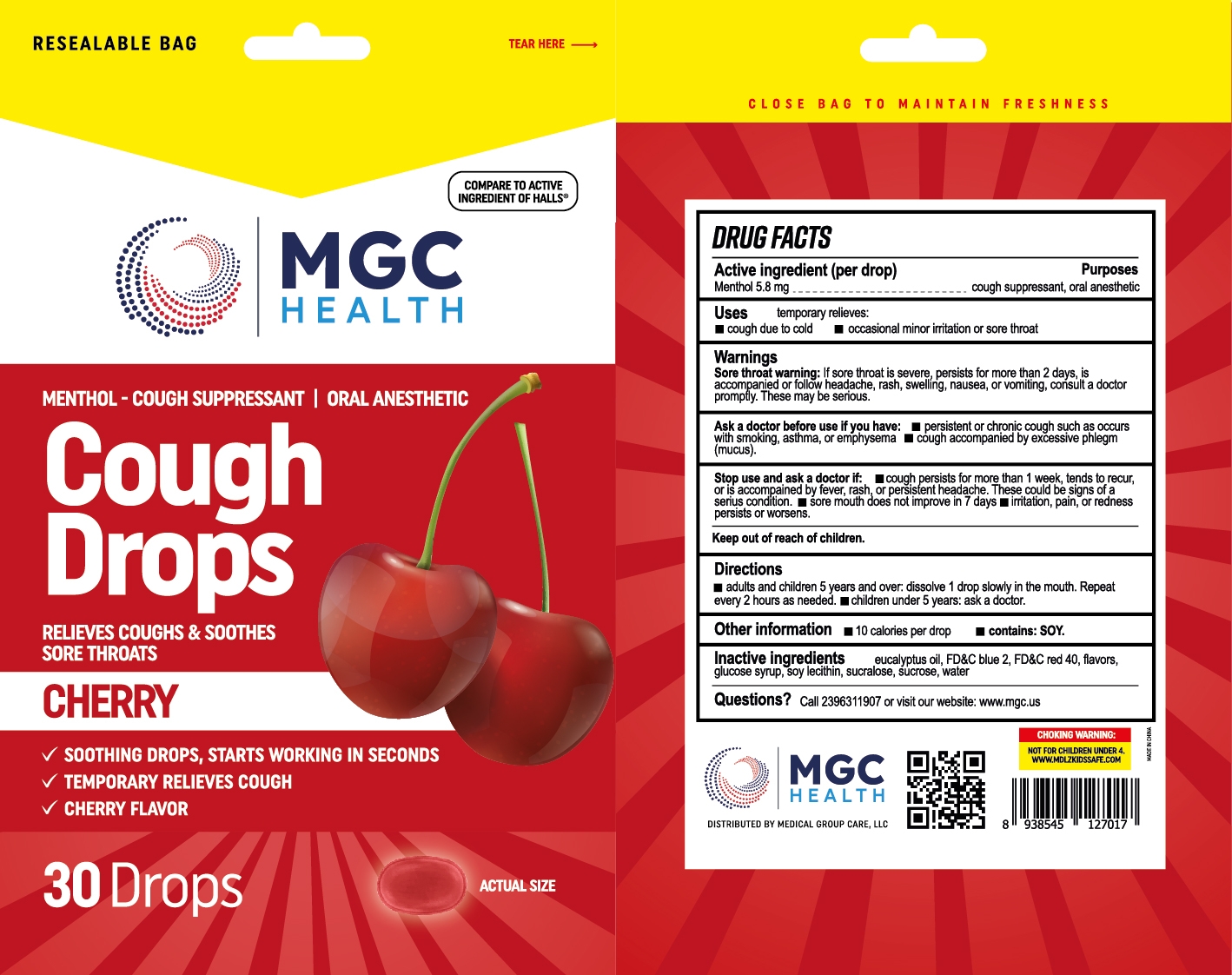 DRUG LABEL: MGC Health
NDC: 83698-121 | Form: LOZENGE
Manufacturer: Xiamen Kang Zhongyuan Biotechnology Co., Ltd.
Category: otc | Type: HUMAN OTC DRUG LABEL
Date: 20251229

ACTIVE INGREDIENTS: MENTHOL 5.8 mg/1 1
INACTIVE INGREDIENTS: SUCRALOSE; WATER; FD&C BLUE NO. 2; LECITHIN, SOYBEAN; FD&C RED NO. 40; CORN SYRUP; SUCROSE; EUCALYPTUS OIL

YNBY- MGC Cherry Cough Drops 30,80- Updated 2023

Active Ingredient(s)

Menthol 5.8 mg

Purpose

Purposes cough suppressant, oral anesthetic

Use

temporary relieves: ■ cough due to cold ■ occasional minor irritation or sore throat

Warnings

Sore throat warning: If sore throat is severe, persists for more than 2 days, is accompanied or follow headache, rash, swelling, nausea, or vomiting, consult a doctor promptly. These may be serious.

Ask a doctor before use if you have: ■ persistent or chronic cough such as occurs with smoking, asthma, or emphysema ■ cough accompanied by excessive phlegm (mucus).

Stop use and ask a doctor if ■ cough persists for more than 1 week, tends to recur, or is accompained by fever, rash, or persistent headache. These could be signs of a serius condition. ■ sore mouth does not improve in 7 days ■ irritation, pain, or redness persists or worsens.

Keep out of reach of children.

Directions

■ adults and children 5 years and over: dissolve 1 drop slowly in the mouth. Repeat every 2 hours as needed.

■ children under 5 years: ask a doctor.

Other information

■ 10 calories per drop ■ contains: SOY.

Inactive ingredients

eucalyptus oil, FD&C blue 2, FD&C red 40, flavors, glucose syrup, soy lecithin, sucralose, sucrose, water

QUESTIONS

Call 2396311907 or visit our website: www.mgc.us

Package Label - Principal Display Panel

30 drops NDC:61658-121-30